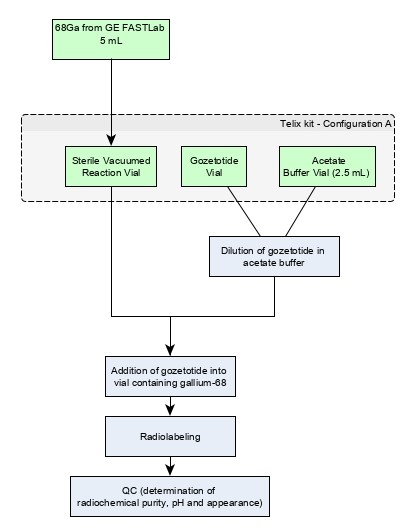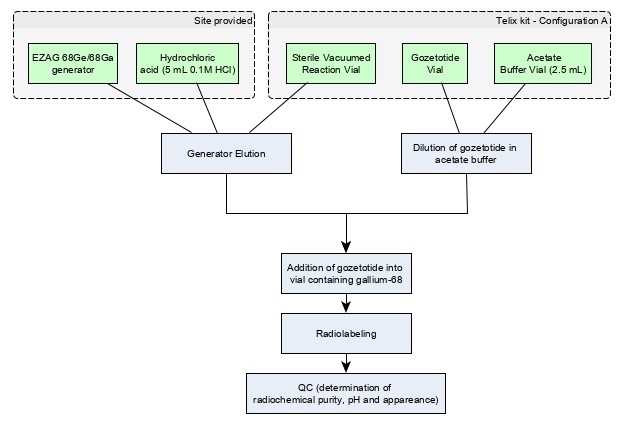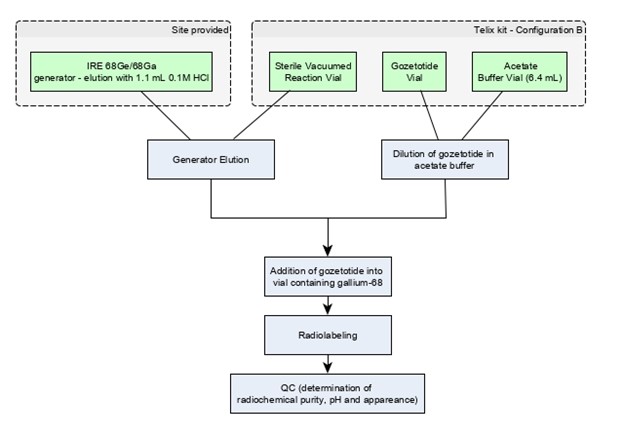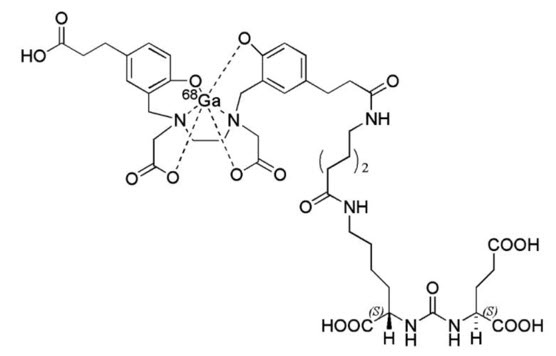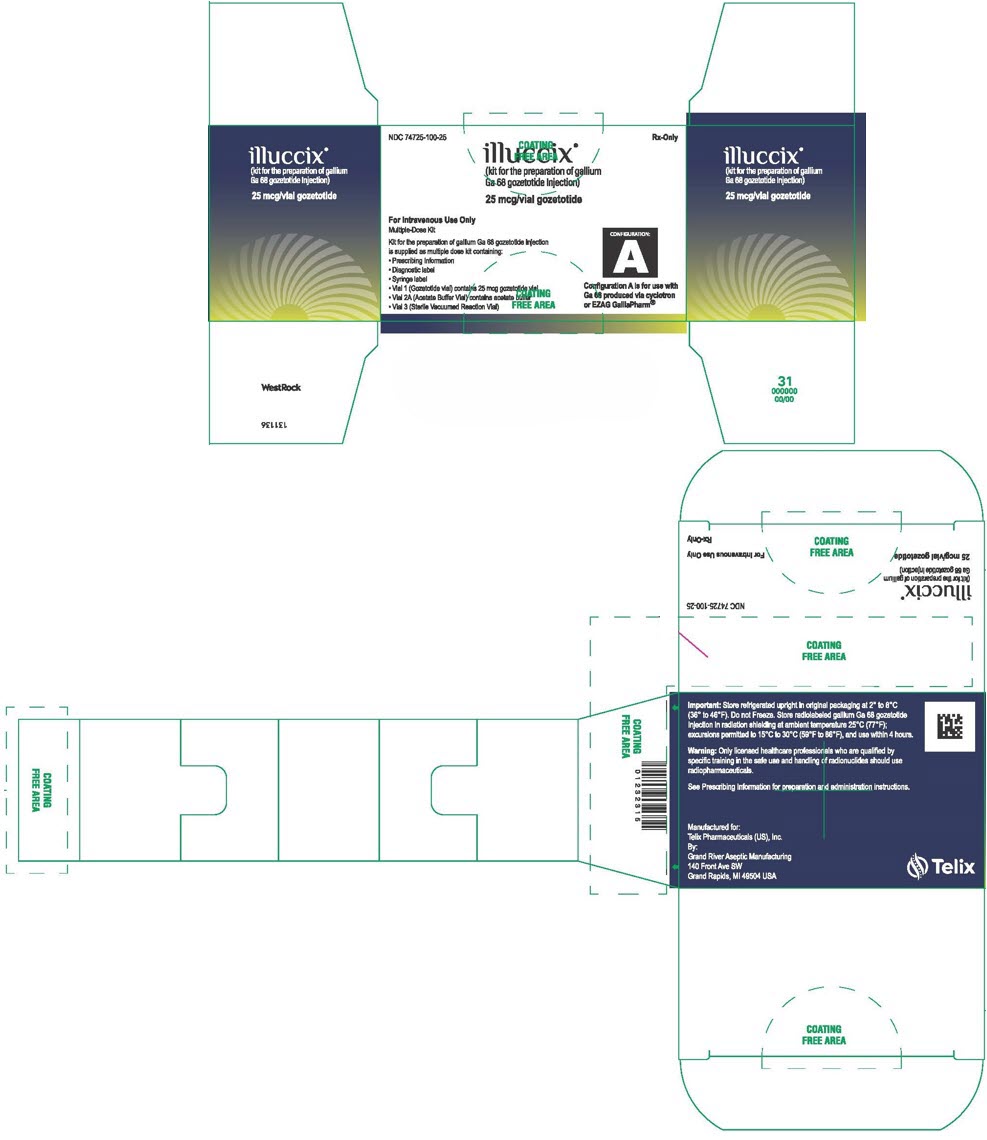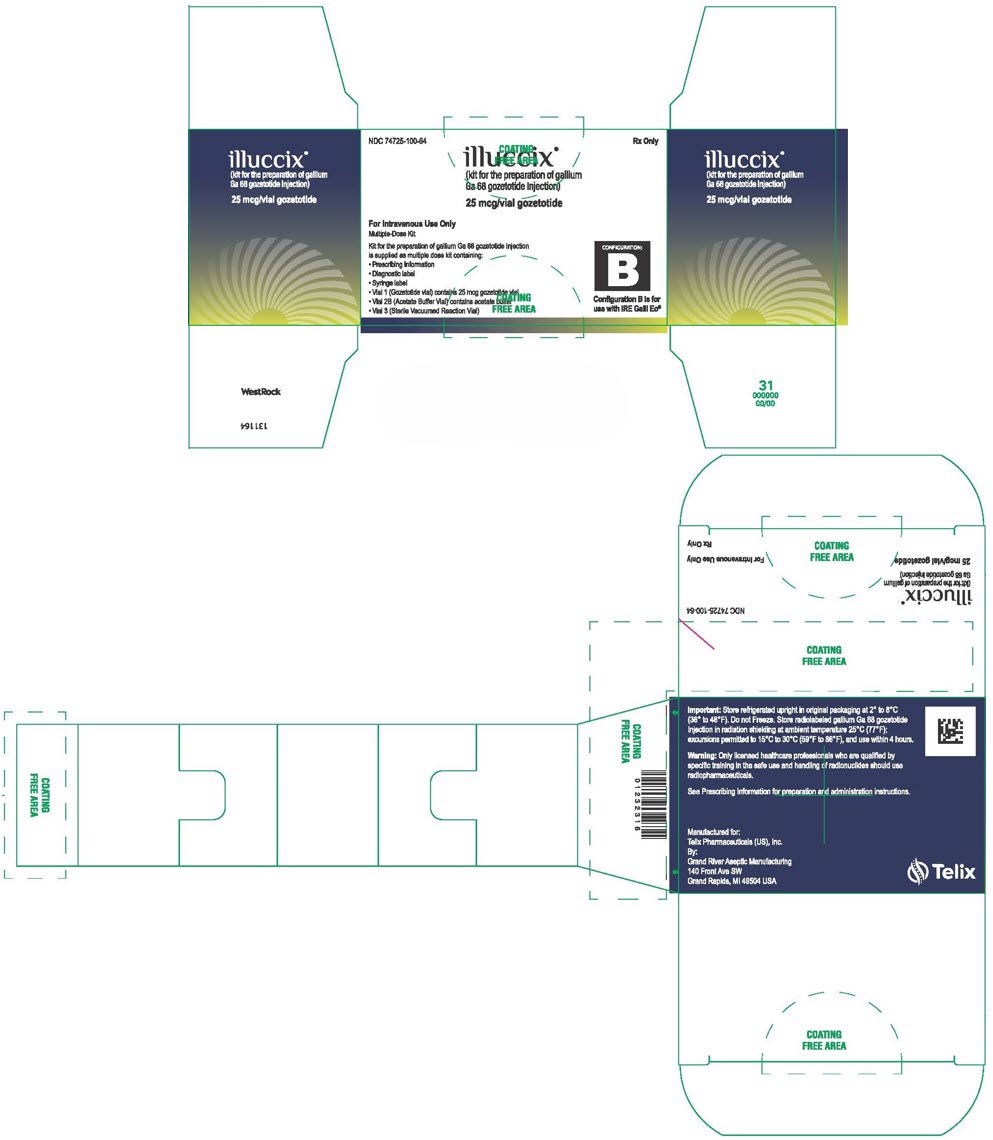 DRUG LABEL: ILLUCCIX
NDC: 74725-100 | Form: KIT | Route: INTRAVENOUS
Manufacturer: Telix Pharmaceuticals (US) Inc.
Category: prescription | Type: HUMAN PRESCRIPTION DRUG LABEL
Date: 20251205

ACTIVE INGREDIENTS: GOZETOTIDE 25 ug/1 1
INACTIVE INGREDIENTS: DEMANNOSE 10 ug/1 1; WATER; SODIUM ACETATE ANHYDROUS 150 mg/2.5 mL; HYDROCHLORIC ACID; WATER; SODIUM ACETATE ANHYDROUS 150 mg/6.4 mL; HYDROCHLORIC ACID

HIGHLIGHTS OF PRESCRIBING INFORMATION

These highlights do not include all the information needed to use ILLUCCIX safely and effectively. See full prescribing information for ILLUCCIX.
ILLUCCIX® (kit for the preparation of gallium Ga 68 gozetotide injection), for intravenous use
Initial U.S. Approval: 2020

RECENT MAJOR CHANGES

Indications and Usage (1) | 9/2025
Dosage and Administration, | 9/2025
Drug Preparation (2.4)
Image Interpretation (2.7)
Warnings and Precautions, Risk for Misinterpretation (5.1) | 9/2025

1 INDICATIONS AND USAGE

ILLUCCIX, after radiolabeling with Ga 68, is a radioactive diagnostic agent indicated for positron emission tomography (PET) of prostate-specific membrane antigen (PSMA) positive lesions in men with prostate cancer:

- With suspected metastasis who are candidates for initial definitive therapy
- With suspected recurrence based on elevated serum prostate-specific antigen (PSA) level
- For selection of patients who are indicated for PSMA-directed therapy as described in the prescribing information of the therapeutic products (1)

2 DOSAGE AND ADMINISTRATION

- Use appropriate aseptic technique and radiation safety handling measures in the manipulation and administration of Gallium Ga 68 Gozetotide Injection. (2.1)
- The recommended amount of radioactivity for adults is 111 MBq to 259 MBq (3 mCi to 7 mCi) as a bolus intravenous injection. (2.2)
- A diuretic expected to act within the uptake time period may be administered at the time of radiotracer injection. (2.2)
- Initiate imaging 50 minutes to 100 minutes after administration. The patient should void immediately prior to initiation of imaging. The scan should begin caudally and proceed cranially. (2.6)
- See full prescribing information for additional preparation, administration, imaging, and radiation dosimetry information. (2)

3 DOSAGE FORMS AND STRENGTHS

ILLUCCIX is supplied as a kit containing:

- Vial 1 (Gozetotide Vial) contains 25 mcg gozetotide and 10 mcg D-mannose (stabilizer) as a lyophilized powder
- Vial 2 (Acetate Buffer Vial) contains acetate buffer, either:
  - Vial 2A in Configuration A for use with cyclotron produced Ga 68 via GE FASTlabTMor EZAG generator
  - Vial 2B in Configuration B for use with IRE generator
- Vial 3 (Sterile Vacuumed Reaction Vial) for the collection of gallium Ga 68 chloride and radiolabeling reaction

After radiolabeling and pH adjustment with acetate buffer and radiolabeling with Ga 68, Vial 3 is a multiple-dose vial containing up to 1,850 MBq (50 mCi) of Gallium Ga 68 Gozetotide Injection in 7.5 mL at a strength of up to 247 MBq (6.7 mCi) per mL. (3)

4 CONTRAINDICATIONS

None (4)

5 WARNINGS AND PRECAUTIONS

- Risk for Misinterpretation: Gallium Ga 68 gozetotide uptake can be seen in a variety of tumor types and in non-malignant processes. Interpretation of ILLUCCIX PET imaging with histopathology and/or other diagnostic procedures is recommended. (5.1)
- Radiation Risks: Ensure safe handling to protect patients and health care providers from unintentional radiation exposure. (2.1, 5.2)

6 ADVERSE REACTIONS

The most commonly reported adverse reactions (incidence ≥ 0.5%) include fatigue, nausea, constipation, and vomiting. (6.1)

To report SUSPECTED ADVERSE REACTIONS, contact Telix Pharmaceuticals (US) Inc. at 1-844-455-8638 or FDA at 1-800-FDA-1088 or www.fda.gov/medwatch.

FULL PRESCRIBING INFORMATION

1 INDICATIONS AND USAGE

ILLUCCIX, after radiolabeling with Ga 68, is indicated for positron emission tomography (PET) of prostate-specific membrane antigen (PSMA) positive lesions in men with prostate cancer:

- With suspected metastasis who are candidates for initial definitive therapy
- With suspected recurrence based on elevated serum prostate-specific antigen (PSA) level
- For selection of patients who are indicated for PSMA-directed therapy as described in the prescribing information of the therapeutic products

2 DOSAGE AND ADMINISTRATION

2.1 Radiation Safety - Drug Handling

After reconstitution and radiolabeling of ILLUCCIX, the vial contains Gallium Ga 68 Gozetotide Injection. Handle Gallium Ga 68 Gozetotide Injection with appropriate safety measures to minimize radiation exposure [ see Warnings and Precautions (5.2)]. Use waterproof gloves, effective radiation shielding, and other appropriate safety measures when preparing and handling Gallium Ga 68 Gozetotide Injection.

Radiopharmaceuticals should be used by or under the control of physicians who are qualified by specific training and experience in the safe use and handling of radionuclides, and whose experience and training have been approved by the appropriate governmental agency authorized to license the use of radionuclides.

2.2 Recommended Dosage and Administration Instructions

Recommended Dosage

In adults, the recommended amount of radioactivity to be administered for PET is 111 MBq to 259 MBq (3 mCi to 7 mCi) administered as an intravenous bolus injection.

Administration

- Use aseptic technique and radiation shielding when withdrawing and administering Gallium Ga 68 Gozetotide Injection.
- Calculate the necessary volume to administer based on calibration time and required dose.
- Inspect Gallium Ga 68 Gozetotide Injection visually for particulate matter and discoloration before administration. Only use solutions that are clear, colorless or at most slightly yellow, and without visible particles.
- Gallium Ga 68 Gozetotide Injection may be diluted with sterile 0.9% Sodium Chloride Injection, USP.
- Assay the final dose in a dose calibrator immediately before administration to the patient.
- After injection of Gallium Ga 68 Gozetotide Injection, administer an intravenous flush of sterile 0.9% Sodium Chloride Injection, USP to ensure full delivery of the dose.
- Dispose of any unused drug in a safe manner in compliance with applicable regulations.
- Unless contraindicated, a diuretic expected to act within the uptake time period may be administered at the time of radiotracer injection to potentially decrease artifact from radiotracer accumulation in the urinary bladder and ureters.

2.3 Patient Preparation Prior to PET Imaging

Instruct patients to drink a sufficient amount of water to ensure adequate hydration prior to administration of Gallium Ga 68 Gozetotide Injection and to continue to drink and void frequently following administration to reduce radiation exposure, particularly during the first hour after administration [see Warnings and Precautions (5.2)].

2.4 Drug Preparation

ILLUCCIX is supplied as a 3-vial kit in two different configurations [see Dosage Forms and Strengths (3)] for preparation of Gallium Ga 68 Gozetotide Injection with eluate from one of the following (see below for specific instructions for use with each Ga 68 source):

- Cyclotron produced via GE FASTlabTM(Configuration A)
- Eckert & Ziegler (EZAG) GalliaPharm®Germanium 68/Gallium 68 (Ge 68/Ga 68) generator (Configuration A)
- IRE Galli Eo®Ge 68/Ga 68 generator (Configuration B)

The Ge 68/Ga 68 generators and cyclotron are not supplied with ILLUCCIX.

Components of ILLUCCIX include:

- Vial 1 (Gozetotide Vial) contains 25 mcg of gozetotide and 10 mcg of D-mannose (stabilizer) as a lyophilized powder.

- Vial 2 (Acetate Buffer Vial) contains 150 mg anhydrous sodium acetate in HCl buffer.
- Vial 3 (Sterile Vacuumed Reaction Vial) is a sterile, evacuated vial that serves as the collection vial for Ga 68 chloride and radiolabeling reaction.

Prepare Gallium Ga 68 Gozetotide Injection according to the following aseptic procedure:

1. Before use, remove the ILLUCCIX kit containing all three components from the refrigerator and allow the kit to reach room temperature for 1 hour.
2. Use suitable shielding to reduce radiation exposure.
3. Wear waterproof gloves.
4. If Ga 68 is generator produced, test the Ga 68 chloride eluate for Ge 68 breakthrough weekly by a suitable method according to manufacturer recommendations. Ge 68 breakthrough and other gamma emitting radionuclides should meet the specifications (≤0.001%) provided by the manufacturer. If Ga 68 is cyclotron produced, test for Ga 66 and Ga 67 (with specification of ≤2% combined total) when a new lot of Zn 68 is introduced for manufacturing.
5. Place a "radioactive" label on Vial 3 (Sterile Vacuumed Reaction Vial) with product name, lot number and date.
6. Remove the vial cap from Vial 1, Vial 2 and Vial 3.
7. Swab the top of each vial with alcohol to disinfect the surface and allow the top of each vial to dry.
8. Note that to minimize any potential metallic contamination, the shortest possible needle should be used for the transfer of the gallium solution from the generator. The needle should be clean and dilute acid resistant.
9. Use only plastic syringes for preparation and administration. Do notuse syringes with rubber plungers.
10. Note that prior to use of any vial, confirm the correct vial is being used by a visual check of the vial label.
11. Follow the specific reconstitution procedure below, dependent on Ga 68 source. Then continue with the dilution and radiosynthesis procedure below.

Preparation with Cyclotron Produced Ga 68 via GE FASTlab

Collection of Gallium Ga 68 Chloride

1. After purification by the FASTlab, the Ga 68 chloride solution is passed through a sterile filter and into the cassette product vial automatically by the FASTlab.
2. Pierce Vial 3 (Sterile Vacuumed Reaction Vial) with a sterile needle connected to a 0.2 micron sterile vented filter (not supplied) to maintain atmospheric pressure within the vial during the reconstitution process.
3. Aseptically transfer 5 mL of Ga 68 chloride solution into Vial 3.

Reconstitution and Radiolabeling Reaction Procedure

1. Insert a sterile 10 mL syringe with a needle into Vial 2 (Acetate Buffer Vial Configuration A) and draw up the contents of the vial (target 2.5 mL).
2. Inject the contents of the 10 mL syringe into Vial 1 (Gozetotide Vial).
3. Gently swirl Vial 1 to ensure the product is thoroughly dissolved.
4. Insert a sterile 10 mL syringe with a needle into Vial 1 containing the dissolved gozetotide and draw up the entire contents of the vial.
5. Transfer the contents of the 10 mL syringe to Vial 3 (Sterile Vacuumed Reaction Vial) containing the Ga 68 chloride.
6. Wait for 5 minutes for radiolabeling to take place at ambient temperature (25°C (77°F); excursions permitted to 15°C to 30°C (59°F to 86°F)).
7. Assay the whole vial containing the Gallium Ga 68 Gozetotide Injection for total radioactivity using a dose calibrator, calculate the radioactivity concentration and record the result.
8. Perform the quality control of Gallium Ga 68 Gozetotide Injection according to the recommended methods in the Subsection 2.5Specifications and Quality Control.
9. Prior to use, visually inspect the solution behind a shielded screen for radioprotection purposes. Only use solutions that are clear without visible particles.
10. Keep the vial containing the Gallium Ga 68 Gozetotide Injection upright in a radio-protective shield container at ambient temperature until use.
11. After reconstitution and addition of Ga 68 chloride to the kit components in the reaction Vial 3, use Gallium Ga 68 Gozetotide Injection within 4 hours. The final volume of the Gallium Ga 68 Gozetotide Injection is 7.5 mL.

Preparation with Eckert & Ziegler GalliaPharm Generator

Collection of Gallium Ga 68 Chloride

1. Prepare a syringe containing 5 mL of sterile ultrapure 0.1 M HCl provided with the GalliaPharm Generator for elution.
2. Pierce Vial 3 (Sterile Vacuumed Reaction Vial) with a sterile needle connected to a 0.2 micron sterile vented filter (not supplied) to maintain atmospheric pressure within the vial during the reconstitution process.
3. Connect the male luer of the outlet line of the GalliaPharm generator to a sterile needle.
4. Connect Vial 3 directly to the outlet line of the GalliaPharm generator by pushing the needle through the rubber septum and place the vial in a radiation shielded container.
5. Elute the generator directly with the 5 mL 0.1 M HCl from step 1 into Vial 3 according to the instructions for use of the GalliaPharm generator that are supplied by Eckert & Ziegler. Perform the elution manually or by means of a pump. Collect 5 mL of eluate.
6. At the end of the elution, disconnect the generator from Vial 3 by removing the needle from the rubber septum.

Reconstitution and Radiolabeling Reaction Procedure

1. Insert a sterile 10 mL syringe with a needle into Vial 2 (Acetate Buffer Vial Configuration A) and draw up the contents of the vial (target 2.5 mL).
2. Inject the contents of the 10 mL syringe into Vial 1 (Gozetotide Vial).
3. Gently swirl Vial 1 to ensure the product is thoroughly dissolved.
4. Insert a sterile 10 mL syringe with a needle into Vial 1 containing the dissolved gozetotide and draw up the entire contents of the vial.
5. Transfer the contents of the 10 mL syringe to Vial 3 (Sterile Vacuumed Reaction Vial) containing the Ga 68 chloride.
6. Wait for 5 minutes for radiolabeling to take place at ambient temperature (25°C (77°F); excursions permitted to 15°C to 30°C (59°F to 86°F)).
7. Assay the whole vial containing the Gallium Ga 68 Gozetotide Injection for total radioactivity using a dose calibrator, calculate the radioactivity concentration and record the result.
8. Perform the quality control of Gallium Ga 68 Gozetotide Injection according to the recommended methods in the Subsection 2.5Specifications and Quality Control.
9. Prior to use, visually inspect the solution behind a shielded screen for radioprotection purposes. Only use solutions that are clear without visible particles.
10. Keep the vial containing the Gallium Ga 68 Gozetotide Injection upright in a radio-protective shield container at ambient temperature until use.
11. After reconstitution and addition of Ga 68 chloride to the kit components in the reaction Vial 3, use Gallium Ga 68 Gozetotide Injection within 4 hours. The final volume of the Gallium Ga 68 Gozetotide Injection is 7.5 mL.

Preparation with IRE Galli Eo Generator

Collection of Gallium Ga 68 Chloride

1. Connect the male luer of the outlet line of the Galli Eo generator to a sterile needle.
2. Elute the generator directly into Vial 3 (Sterile Vacuumed Reaction Vial) according to the instructions for use of the Galli Eo generator that are supplied by IRE. Collect 1.1 mL of eluate.
3. At the end of the elution, disconnect the generator from Vial 3 by removing the needle from the rubber septum.

Reconstitution and Radiolabeling Reaction Procedure

1. Insert a sterile 10 mL syringe with a needle into Vial 2 (Acetate Buffer Vial Configuration B) and draw up the contents of the vial (target 6.4 mL).
2. Inject the contents of the 10 mL syringe into Vial 1 (Gozetotide Vial).
3. Gently swirl Vial 1 to ensure the product is thoroughly dissolved.
4. Insert a sterile 10 mL syringe with a needle into Vial 1 containing the dissolved gozetotide and draw up the entire contents of the vial.
5. Transfer the contents of the 10 mL syringe to Vial 3 (Sterile Vacuumed Reaction Vial) containing the Ga 68 chloride.
6. Wait for 5 minutes for radiolabeling to take place at ambient temperature (25°C (77°F); excursions permitted to 15°C to 30°C (59°F to 86°F)).
7. Assay the whole vial containing the Gallium Ga 68 Gozetotide Injection for total radioactivity using a dose calibrator, calculate the radioactivity concentration and record the result.
8. Perform the quality control of Gallium Ga 68 Gozetotide Injection according to the recommended methods in the Subsection 2.5Specifications and Quality Control.
9. Prior to use, visually inspect the solution behind a shielded screen for radioprotection purposes. Only use solutions that are clear without visible particles.
10. Keep the vial containing the Gallium Ga 68 Gozetotide Injection upright in a radio-protective shield container at ambient temperature until use.
11. After reconstitution and addition of Ga 68 chloride to the kit components in the reaction Vial 3, use Gallium Ga 68 Gozetotide Injection within 4 hours. The final volume of the Gallium Ga 68 Gozetotide Injection is 7.5 mL.

Flow diagrams are provided for the radiosynthetic process to be followed at the radiopharmacy site for:

- ILLUCCIX Configuration "A" when using Ga 68 prepared by cyclotron (Figure 1) or
- ILLUCCIX Configurations "A" or "B" when using an indicated GMP-grade EZAG GalliaPharm Ge 68/Ga 68 Generator (Figure 2) or IRE Galli Eo Ge 68/Ga 68 Generator (Figure 3).

Figure 1: Preparation with Cyclotron Produced Ga 68 via GE FASTlab

Note: Ga 68 from GE FASTlab is aseptically transferred into the Sterile Vacuumed Reaction Vial.

Use "Configuration A" with cyclotron produced Ga 68 via GE FASTlab [see How Supplied/Storage and Handling (16)].

Figure 2: Preparation with Eckert & Ziegler GalliaPharm Generator

Note: Use "Configuration A" with EZAG GalliaPharm Ge 68/Ga 68 generator [see How Supplied/Storage and Handling (16)].

Figure 3: Preparation with IRE Galli Eo Generator

Note: Use "Configuration B" with IRE Galli Eo Ge 68/Ga 68 generator [see How Supplied/Storage and Handling (16)].

2.5 Specifications and Quality Control

Perform the quality controls in Table 1behind a lead glass shield for radioprotection purposes.

Table 1: Specifications for the Radiolabeled Imaging Product (Gallium Ga 68 Gozetotide Injection)

Test | Analytical method | Acceptance criteria
Appearance | Visual examination | Colorless to slightly yellow solution; Free from visible particles
pH | pH-meter or pH-strips | 4.0 to 5.0
Radiochemical purity; - Content of gallium Ga 68 gozetotide - Content of free and colloidal Ga 68 | Instant thin-layer chromatography, silica gel (iTLC SG); See methods below | ≥95% ≤5%

Perform one of the following:

Cutting Technique

1. Pour ammonium acetate 1 M/methanol (1/1 V/V) solution to a depth of 3 mm to 4 mm in the developing chamber, cover the chamber and allow it to equilibrate.
2. Draw a pencil line at 1 cm from the bottom of the iTLC strip, and a dotted line 5 cm from the pencil line. Apply a drop of gallium Ga 68 gozetotide at the center of the pencil line.
3. Place the iTLC strip in the developing chamber and allow it to develop for a distance of 10 cm from the point of application.

1. Cut the iTLC strip following the dotted line and measure each piece with the radioactivity dose calibrator.
2. Calculate the quantity (in percent) of gallium Ga 68 gozetotide in the solution using the formula:

% Gallium Ga 68 gozetotide=(Activity top piece)/(Activity bottom piece+Activity top piece) ×100

Scanning Technique

1. Pour ammonium acetate 1 M/methanol (1/1 V/V) solution to a depth of 3 mm to 4 mm in the developing chamber, cover the chamber and allow it to equilibrate.
2. Draw a pencil line at 1 cm from the bottom of the iTLC strip and apply a drop of gallium Ga 68 gozetotide at the center of the pencil line.
3. Place the iTLC strip in the developing chamber and allow it to develop for a distance of 10 cm from the point of application.
4. Scan the iTLC with a radiometric iTLC scanner.

1. Calculate the quantity (in percent) of gallium Ga 68 gozetotide in the solution by integration of the peaks on the chromatogram.
2. The retention factor (Rf) specifications are:

Free and colloidal Ga 68 species, Rf = 0 to 0.1,

Gallium Ga 68 gozetotide, Rf = 0.6 to 1.

2.6 Image Acquisition

Position the patient supine with arms above the head. Begin PET scanning 50 minutes to 100 minutes after the intravenous administration of Gallium Ga 68 Gozetotide Injection. Patients should void immediately prior to image acquisition and image acquisition should begin at the proximal thighs and proceed cranially to the skull base or skull vertex. Adapt imaging technique according to the equipment used and patient characteristics in order to obtain the best image quality possible.

2.7 Image Interpretation

Gallium Ga 68 gozetotide binds to PSMA. Based on the intensity of the signals, PET images obtained using gallium Ga 68 gozetotide indicate the presence of PSMA in tissues.

Imaging Prior to Initial Definitive Therapy or for Biochemical Recurrence

Lesions should be considered suspicious if uptake is greater than physiologic uptake in that tissue or greater than adjacent background if no physiologic uptake is expected. Tumors that do not express PSMA will not be visualized. Increased uptake in tumors is not specific for prostate cancer [ see Warnings and Precautions (5.1) ].

Imaging to Select Patients for PSMA-Directed Therapy

For instructions on patient selection, refer to the prescribing information of the PSMA-directed therapeutic product.

2.8 Radiation Dosimetry

Estimated radiation absorbed doses per injected activity for organs and tissues of adult male patients following an intravenous bolus of Gallium Ga 68 Gozetotide Injection are shown in Table 2.

The effective radiation dose resulting from the administration of 259 MBq (7 mCi) is about 4.4 mSv. The radiation doses for this administered dose to the critical organs, which are the kidneys, urinary bladder, and spleen, are 96.2 mGy, 25.4 mGy, and 16.8 mGy, respectively.

These radiation doses are for Gallium Ga 68 Gozetotide Injection alone. If CT or a transmission source are used for attenuation correction, the radiation dose will increase by an amount that varies by technique.

Table 2: Estimated Radiation Absorbed Dose per Injected Activity in Selected Organs and Tissues of Adults after Intravenous Administration of Gallium Ga 68 Gozetotide Injection

Organ | Absorbed dose (mGy/MBq)
Organ | Mean | SD
Adrenals | 0.0156 | 0.0014
Brain | 0.0104 | 0.0011
Breasts | 0.0103 | 0.0011
Gallbladder | 0.0157 | 0.0012
Lower Colon | 0.0134 | 0.0009
Small Intestine | 0.014 | 0.002
Stomach | 0.0129 | 0.0008
Heart | 0.012 | 0.0009
Kidneys | 0.3714 | 0.0922
Liver | 0.0409 | 0.0076
Lungs | 0.0111 | 0.0007
Muscle | 0.0103 | 0.0003
Pancreas | 0.0147 | 0.0009
Red Marrow | 0.0114 | 0.0016
Skin | 0.0091 | 0.0003
Spleen | 0.065 | 0.018
Testes | 0.0111 | 0.0006
Thymus | 0.0105 | 0.0006
Thyroid | 0.0104 | 0.0006
Urinary Bladder | 0.0982 | 0.0286
Total Body | 0.0143 | 0.0013
Effective Dose (mSv/MBq) | 0.0169 | 0.0015

3 DOSAGE FORMS AND STRENGTHS

ILLUCCIX is supplied as a kit for the preparation of Gallium Ga 68 Gozetotide Injection. Each kit contains:

- Vial 1 (Gozetotide Vial): 25 mcg of gozetotide and 10 mcg of D-mannose (stabilizer) as a lyophilized powder.
- Vial 2 (Acetate Buffer Vial): 150 mg anhydrous sodium acetate in HCl buffer, provided as either vial 2A or vial 2B, depending on Ga 68 source used.
- Vial 3 (Sterile Vacuumed Reaction Vial): a sterile, evacuated vial that serves as the collection vial for Ga 68 chloride and radiolabeling reaction.

Ga 68 is obtained from one of the following sources:

- Cyclotron via GE FASTlab.
- Eckert & Ziegler GalliaPharm Ge 68/Ga 68 generator
- IRE Galli Eo Ge 68/Ga 68 generator.

After reconstitution and pH adjustment with acetate buffer and radiolabeling with Ga 68, Vial 3 is a multiple-dose vial containing up to 1,850 MBq (50 mCi) of Gallium Ga 68 Gozetotide Injection in 7.5 mL at a strength of up to 247 MBq (6.7 mCi) per mL.

4 CONTRAINDICATIONS

None

5 WARNINGS AND PRECAUTIONS

5.1 Risk for Misinterpretation

Image interpretation errors can occur with ILLUCCIX PET. A negative image does not rule out the presence of prostate cancer and a positive image does not confirm the presence of prostate cancer. Gallium Ga 68 gozetotide uptake is not specific for prostate cancer and may occur with other types of cancer as well as non-malignant processes such as Paget's disease, fibrous dysplasia, and osteophytosis. Clinical correlation, which may include histopathological evaluation of the suspected prostate cancer site, is recommended.

The performance of ILLUCCIX for imaging of biochemically recurrent prostate cancer seems to be affected by serum PSA levels and by site of disease. The performance of ILLUCCIX for imaging of metastatic pelvic lymph nodes prior to initial definitive therapy seems to be affected by Gleason score [see Clinical Studies (14.1, 14.2)] .

5.2 Radiation Risks

Gallium Ga 68 gozetotide contributes to a patient's overall long-term cumulative radiation exposure. Long-term cumulative radiation exposure is associated with an increased risk for cancer. Ensure safe handling to minimize radiation exposure to the patient and health care providers. Advise patients to hydrate before and after administration and to void frequently after administration [see Dosage and Administration (2.1,2.3)].

6 ADVERSE REACTIONS

6.1 Clinical Trials Experience

Because clinical trials are conducted under widely varying conditions, adverse reaction rates observed in the clinical trials of a drug cannot be directly compared to rates in the clinical trials of another drug and may not reflect the rates observed in practice.

The safety of ILLUCCIX has been established based on three prospective studies of gallium Ga 68 gozetotide in patients with prostate cancer (i.e., Studies 1, 2, and 3). Adverse reactions from these studies are reported below.

In Studies 1 and 2 using another formulation of gallium Ga 68 gozetotide injection, 960 patients received one dose of gallium Ga 68 gozetotide intravenously with the amount (mean ± SD) of radioactivity 188.7 ± 40.7 MBq (5.1 ± 1.1 mCi) [ see Clinical Studies (14.1, 14.2) ]. The most commonly reported adverse reactions were nausea, diarrhea, and dizziness, occurring at a rate of <1%.

In a randomized, multicenter, open-label clinical study (NCT03511664, referred to as Study 3) in which gallium Ga 68 gozetotide was used to identify PSMA-positive patients on PET imaging to determine eligibility for PSMA-directed therapy, 1,003 patients with progressive metastatic castration-resistant prostate cancer (mCRPC) received one dose of gallium Ga 68 gozetotide intravenously with the amount of radioactivity 167.1 ± 23.1 MBq (4.52 ± 0.62 mCi). Patients were males with median age of 70 years (range, 40 to 94 years), were White (87%), Black or African American (7%), or Asian (2.4%), and had median baseline PSA levels of 74 ng/mL (range, 0 to 8,995 ng/mL).

Adverse reactions occurring at ≥ 0.5% in patients with metastatic prostate cancer who received gallium Ga 68 gozetotide injection in Study 3 are presented in Table 3.

Table 3: Adverse Reactions (≥ 0.5%) in Patients with Metastatic Prostate Cancer Who Received Gallium Ga 68 Gozetotide Injection in Study 3

Adverse Reaction | Gallium Ga 68 Gozetotide Injection; N = 1,003; n (%)
General disorders
Fatigue | 12 (1.2)
Gastrointestinal disorders
Nausea | 8 (0.8)
Constipation | 5 (0.5)
Vomiting | 5 (0.5)

Adverse reactions occurring at a rate of < 0.5% in the study were diarrhea, dry mouth, injection site reactions, including injection site hematoma and injection site warmth and chills.

6.2 Postmarketing Experience

The following adverse reactions have been identified during postapproval use of ILLUCCIX. Because these reactions are reported voluntarily from a population of uncertain size, it is not always possible to reliably estimate their frequency or establish a causal relationship to drug exposure.

General Disorders and Administration Site Conditions: injection site pain.

7 DRUG INTERACTIONS

Androgen deprivation therapy and other therapies targeting the androgen pathway

Androgen deprivation therapy (ADT) and other therapies targeting the androgen pathway, such as androgen receptor antagonists, can result in changes in uptake of gallium Ga 68 gozetotide in prostate cancer. The effect of these therapies on performance of gallium Ga 68 gozetotide PET has not been established.

8 USE IN SPECIFIC POPULATIONS

8.1 Pregnancy

Risk Summary

ILLUCCIX is not indicated for use in females. There are no available data with gallium Ga 68 gozetotide injection use in pregnant women to evaluate for a drug-associated risk of major birth defects, miscarriage, or adverse maternal or fetal outcomes. All radiopharmaceuticals, including ILLUCCIX, have the potential to cause fetal harm depending on the fetal stage of development and the magnitude of the radiation dose. Animal reproduction studies have not been conducted with gallium Ga 68 gozetotide.

8.2 Lactation

Risk Summary

ILLUCCIX is not indicated for use in females. There are no data on the presence of gallium Ga 68 gozetotide in human milk, the effect on the breastfed infant, or the effect on milk production.

8.4 Pediatric Use

The safety and effectiveness of gallium Ga 68 gozetotide in pediatric patients have not been established.

8.5 Geriatric Use

The efficacy of gallium Ga 68 gozetotide PET in geriatric patients with prostate cancer is based on data from three prospective studies.

Of the total number of patients in Studies 1 and 2 [see Clinical Studies (14.1, 14.2)] , 691 of 960 (72%) patients were 65 years of age and older while 195 (20%) were 75 years of age and older.

Of the total number of patients in Study 3 [ see Adverse Reactions (6.1)], 752 of 1,003 (75%) patients were 65 years of age and older while 284 (28%) were 75 years of age and older.

The efficacy and safety profiles of gallium Ga 68 gozetotide appear similar in younger adult and geriatric patients with prostate cancer and other reported clinical experience has not identified differences in responses between the elderly and younger adult patients.

10 OVERDOSAGE

In the event of an overdose of gallium Ga 68 gozetotide, reduce the radiation absorbed dose to the patient where possible by increasing the elimination of the drug from the body using hydration and frequent bladder voiding. A diuretic might also be considered. If possible, an estimate of the radiation effective dose given to the patient should be made.

11 DESCRIPTION

11.1 Chemical Characteristics

ILLUCCIX, a radioactive diagnostic agent, is supplied as a sterile, multiple-dose kit for the preparation of Gallium Ga 68 Gozetotide Injection for intravenous use. Gozetotide is also known as PSMA-11.

Gallium Ga 68 gozetotide is a radioconjugate composed of a human prostate specific membrane antigen (PSMA)-targeting ligand peptide conjugated via the acyclic radiometal chelator, N,N'-bis [2-hydroxy-5-(carboxyethyl)benzyl] ethylenediamine-N,N'-diacetic acid (HBED-CC) to the radioisotope Ga 68. The amino acid sequence of the gozetotide peptide is Glu-NH-CO-NH-Lys(Ahx), (Ahx = 6-aminohexanoic acid). Gallium Ga 68 gozetotide has a molecular weight of 1011.9 g/mol and its chemical structure is shown in Figure 4.

Figure 4: Chemical Structure of Gallium Ga 68 Gozetotide

11.2 Physical Characteristics

ILLUCCIX is supplied as a 3-vial kit which contains the non-radioactive ingredients needed to produce Gallium Ga 68 Gozetotide Injection. There are two configurations available to allow preparation of Gallium Ga 68 Gozetotide Injection using Ga 68 from different generator or cyclotron sources [ see How Supplied/Storage and Handling (16) ]. The prepared Gallium Ga 68 Gozetotide Injection for intravenous use is a sterile, pyrogen free, clear, colorless, buffered solution with a pH between 4.0 to 5.0.

11.3 External Radiation

Table 4, Table 5, and Table 6display the principal radiation emission data, radiation attenuation by lead shielding, and physical decay of Ga 68.

Table 4: Principal Radiation Emission Data (>1%)

Radiation/ Emission | % Disintegration | Mean Energy (MeV)
beta+ | 88% | 0.8360
beta+ | 1.1% | 0.3526
gamma | 178% | 0.5110
gamma | 3.0% | 1.0770
X-ray | 2.8% | 0.0086
X-ray | 1.4% | 0.0086

Table 5: Radiation Attenuation of 511 keV Photons by Lead (Pb) Shielding

Shield Thickness (Pb) mm | Coefficient of Attenuation
6 | 0.5
12 | 0.25
17 | 0.1
34 | 0.01
51 | 0.001

Table 6: Physical Decay Chart for Ga 68

Minutes | Fraction Remaining
0 | 1
15 | 0.858
30 | 0.736
60 | 0.541
90 | 0.398
120 | 0.293
180 | 0.158
360 | 0.025

12 CLINICAL PHARMACOLOGY

12.1 Mechanism of Action

Gallium Ga 68 gozetotide binds to PSMA. It binds to cells that express PSMA, including malignant prostate cancer cells, which usually overexpress PSMA. Gallium 68 (Ga 68) is a β+ emitting radionuclide that allows positron emission tomography.

12.2 Pharmacodynamics

The relationship between gallium Ga 68 gozetotide plasma concentrations and successful imaging was not explored in clinical trials.

12.3 Pharmacokinetics

Distribution

Intravenously injected gallium Ga 68 gozetotide is cleared from the blood and is accumulated preferentially in the liver (15%), kidneys (7%), spleen (2%), and salivary glands (0.5%). Gallium Ga 68 gozetotide uptake is also seen in the adrenals and prostate. There is no uptake in the cerebral cortex or in the heart, and usually lung uptake is low.

Elimination

A total of 14% of the injected dose is excreted in urine in the first 2 hours post-injection.

13 NONCLINICAL TOXICOLOGY

13.1 Carcinogenesis, Mutagenesis, Impairment of Fertility

No long-term animal studies were performed to evaluate the carcinogenicity potential of gallium Ga 68 gozetotide.

14 CLINICAL STUDIES

14.1 Imaging Prior to Initial Definitive Therapy

The efficacy of ILLUCCIX for PET of PSMA-positive lesions in men with prostate cancer with suspected metastasis who are candidates for initial definitive therapy has been established based on a study of another formulation of gallium Ga 68 gozetotide. Below is a display of the results of the prospective, open label study PSMA-PreRP (NCT03368547 and NCT02919111, referred to as Study 1).

This two-center study enrolled 325 patients with biopsy-proven prostate cancer who were considered candidates for prostatectomy and pelvic lymph node dissection. All enrolled patients met at least one of the following criteria: serum prostate-specific antigen (PSA) of at least 10 ng/mL, tumor stage cT2b or greater, or Gleason score greater than 6. Each patient received a single gallium Ga 68 gozetotide PET/CT or PET/MR from mid-thigh to skull base.

A total of 123 patients (38%) proceeded to standard-of-care prostatectomy and template pelvic lymph node dissection and had sufficient histopathology data for evaluation (evaluable patients). Three members of a pool of six central readers independently interpreted each PET scan for the presence of abnormal gallium Ga 68 gozetotide uptake in pelvic lymph nodes located in the common iliac, external iliac, internal iliac, and obturator subregions bilaterally as well as in any other pelvic location. The readers were blinded to all clinical information except for the history of prostate cancer prior to definitive treatment. Extrapelvic sites and the prostate gland itself were not analyzed in this study. For each patient, gallium Ga 68 gozetotide PET results and reference standard histopathology obtained from dissected pelvic lymph nodes were compared by region (left hemipelvis, right hemipelvis, and other).

For the 123 evaluable patients, the mean age was 65 years (range 45 to 76 years), and 89% were White. The median serum PSA was 11.8 ng/mL. The summed Gleason score was 7 for 44%, 8 for 20%, and 9 for 31% of the patients, with the remainder of the patients having Gleason scores of 6 or 10.

Table 7compares majority PET reads to pelvic lymph node histopathology results at the patient-level with region matching, such that at least one true positive region defines a true positive patient. As shown, approximately 24% of subjects studied were found to have pelvic nodal metastases based on histopathology (95% confidence interval: 17%, 32%).

Table 7: Patient-Level Performance of Gallium Ga 68 Gozetotide PET for Detection of Pelvic Lymph Node Metastasis* in Men with Prostate Cancer with Suspected Metastasis in Study 1 (n=123)

 |  | Histopathology |  | Predictive value**; (95% CI)
 |  | Positive | Negative | Predictive value**; (95% CI)
PET scan | Positive | 14 | 9 | PPV; 61% (41%, 81%)
PET scan | Negative | 16 | 84 | NPV; 84% (79%, 91%)
Total |  | 30 | 93
Diagnostic performance (95% CI) |  | Sensitivity; 47% (29%, 65%) | Specificity; 90% (84%, 96%)

*with region matching where at least one true positive region defines a true positive patient

**PPV: positive predictive value, NPV: negative predictive value

Among the pool of six readers, sensitivity ranged from 36% to 60%, specificity from 83% to 96%, positive predictive value from 38% to 80%, and negative predictive value from 80% to 88%.

In an exploratory subgroup analysis based on summed Gleason score, there was a numerical trend toward more true positives in patients with Gleason score of 8 or higher compared to those with Gleason score of 7 or lower.

An exploratory analysis was performed to estimate the sensitivity and specificity for pelvic nodal metastasis detection in all scanned patients, including the patients who were lacking histopathology reference standard. An imputation method was used based on patient-specific factors. This exploratory analysis resulted in an imputed sensitivity of 47%, with a 95% confidence interval ranging from 38% to 55%, and an imputed specificity of 74%, with a 95% confidence interval ranging from 68% to 80% for all patients imaged with gallium Ga 68 gozetotide PET.

14.2 Imaging of Biochemical Recurrence

The efficacy of ILLUCCIX for PET of PSMA-positive lesions in men with prostate cancer with suspected recurrence based on elevated serum PSA level has been established based on a study of another formulation of gallium Ga 68 gozetotide. Below is a display of the results of the prospective, open label study PSMA-BCR (NCT02940262 and NCT02918357, referred to as Study 2).

This two-center study enrolled 635 patients with biochemical evidence of recurrent prostate cancer after definitive therapy, defined by serum PSA of >0.2 ng/mL more than 6 weeks after prostatectomy or by an increase in serum PSA of at least 2 ng/mL above nadir after definitive radiotherapy. All patients received a single gallium Ga 68 gozetotide PET/CT or PET/MR from mid-thigh to skull base. Three members of a pool of nine independent central readers evaluated each scan for the presence and regional location (20 subregions grouped into four regions) of abnormal gallium Ga 68 gozetotide uptake suggestive of recurrent prostate cancer. The readers were blinded to all clinical information other than type of primary therapy and most recent serum PSA level.

A total of 469 patients (74%) had at least one positive region detected by gallium Ga 68 gozetotide PET majority read. The distribution of gallium Ga 68 gozetotide PET positive regions was 34% bone, 25% prostate bed, 25% pelvic lymph node, and 17% extrapelvic soft tissue. Two hundred and ten patients had composite reference standard information collected in a PET positive region (evaluable patients), consisting of at least one of the following: histopathology, imaging (bone scintigraphy, CT, or MRI) acquired at baseline or within 12 months after gallium Ga 68 gozetotide PET, or serial serum PSA. Composite reference standard information for gallium Ga 68 gozetotide PET negative regions was not systematically collected in this study.

In the 210 evaluable patients, the mean age was 70 years (range 49 to 88 years) and 82% were 65 years of age or older. White patients made up 90% of the group. The median serum PSA was 3.6 ng/mL. Prior treatment included radical prostatectomy in 64% and radiotherapy in 73%.

Of the 210 evaluable patients, 192 patients (91%) were found to be true positive in one or more regions against the composite reference standard (95% confidence interval: 88%, 95%). Among the pool of nine readers used in the study, the proportion of patients who were true positive in one or more regions ranged from 82% to 97%. The prostate bed had the lowest proportion of true positive results at the region-level (76% versus 96% for non-prostate regions).

An exploratory analysis was also performed in which gallium Ga 68 gozetotide PET positive patients who lacked reference standard information were imputed using an estimated likelihood that at least one location-matched PET positive lesion was reference standard positive based on patient-specific factors. In this exploratory analysis, 340 of 475 patients (72%) were imputed as true positive in one or more regions (95% confidence interval: 68%, 76%).

In another exploratory analysis using the same imputation approach for PET positive patients who lacked reference standard information, 340 of 635 patients (54%) were correctly detected as true positive (95% confidence interval: 50%, 57%) among all BCR patients who received a PET scan, whether it was read as positive or negative.

The likelihood of identifying a gallium Ga 68 gozetotide PET positive lesion in this study increased with higher serum PSA level. Table 8shows the patient-level gallium Ga 68 gozetotide PET results stratified by serum PSA level. The mean time between PSA measurement and PET scan was 40 days with a range of 0 to 367 days. Percent PET positivity was calculated as the proportion of patients with a positive gallium Ga 68 gozetotide PET out of all patients scanned. Percent PET positivity includes patients determined to be either true positive or false positive as well as those in whom such determination was not made due to the absence of composite reference standard data.

Table 8: Patient-Level Gallium Ga 68 Gozetotide PET Results and Percent PET Positivity Stratified by Serum PSA Level in Men with Prostate Cancer with Suspected Recurrence in Study 2 (n=628)*

PSA (ng/mL) | PET positive patients |  |  |  | PET negative patients | Percent PET positivity***; (95% CI)
PSA (ng/mL) | Total | TP** | FP** | Without reference standard | PET negative patients | Percent PET positivity***; (95% CI)
PSA (ng/mL) | Total | With reference standard |  | Without reference standard | PET negative patients | Percent PET positivity***; (95% CI)
<0.5 | 48 | 11 | 1 | 36 | 87 | 36%; (27%, 44%)
<0.5 | 48 | 12 |  | 36 | 87 | 36%; (27%, 44%)
≥0.5 and <1 | 44 | 15 | 3 | 26 | 35 | 56%; (45%, 67%)
≥0.5 and <1 | 44 | 18 |  | 26 | 35 | 56%; (45%, 67%)
≥1 and <2 | 71 | 29 | 1 | 41 | 15 | 83%; (75%, 91%)
≥1 and <2 | 71 | 30 |  | 41 | 15 | 83%; (75%, 91%)
≥2 | 299 | 137 | 13 | 149 | 29 | 91%; (88%, 94%)
≥2 | 299 | 150 |  | 149 | 29 | 91%; (88%, 94%)
Total | 462 | 192 | 18 | 252 | 166 | 74%; (70%, 77%)
Total | 462 | 210 |  | 252 | 166 | 74%; (70%, 77%)

*7 patients were excluded from this table due to protocol deviations

**TP: true positive, FP: false positive

***Percent PET positivity = PET positive patients/total patients scanned

14.3 Imaging to Select Patients for PSMA-Directed Therapy

Refer to the prescribing information of the PSMA-directed therapy for description of the studies in which the efficacy of gallium Ga 68 gozetotide for selecting patients has been established.

16 HOW SUPPLIED/STORAGE AND HANDLING

How Supplied

ILLUCCIX is supplied as a kit for preparing Gallium Ga 68 Gozetotide Injection. There are two different kit configurations, each containing 3 vials.

ILLUCCIX Configuration "A" (NDC 74725-100-25) is intended for use with Ga 68 produced from a cyclotron and purified via GE FASTlab or Eckert & Ziegler GalliaPharm Ge 68/Ga 68 generator and includes:

- Vial 1 (Gozetotide Vial): contains 25 mcg gozetotide and 10 mcg D-mannose as a lyophilized powder in a sterile 10 mL vial with a blue flip-off cap (NDC 74725-101-25).
- Vial 2 (Acetate Buffer Vial, Configuration A): contains 150 mg anhydrous sodium acetate in 0.292 M HCl solution (2.5 mL volume) in a sterile 10 mL vial with a red flip off cap (NDC 74725-102-25).
- Vial 3 (Sterile Vacuumed Reaction Vial): an evacuated sterile vial with white flip off cap used to collect Ga 68 chloride from generators or cyclotron and radiolabeling reaction; a multiple-dose vial after radiolabeling.

ILLUCCIX Configuration "B" (NDC 74725-100-64) is intended for use with Ga 68 produced from an IRE Galli Eo Ge 68/Ga 68 generator and includes:

- Vial 1 (Gozetotide Vial): contains 25 mcg gozetotide and 10 mcg D-mannose as a lyophilized powder in a sterile 10 mL vial with a blue flip-off cap (NDC 74725-101-25).
- Vial 2 (Acetate Buffer Vial, Configuration B): contains 150 mg anhydrous sodium acetate in 0.175 M HCl solution (6.4 mL volume) in a sterile 10 mL vial with a green flip off cap (NDC 74725-103-64).
- Vial 3 (Sterile Vacuumed Reaction Vial): an evacuated sterile vial with white flip off cap used to collect Ga 68 chloride from generator and radiolabeling reaction; a multiple-dose vial after radiolabeling.

The radionuclide is not part of the kit. Before radiolabeling with Ga 68, the contents of this kit are not radioactive.

Storage and Handling

Store ILLUCCIX refrigerated upright in the original packaging at 2° to 8°C (36° to 46°F). Do not freeze.

After radiolabeling, keep Gallium Ga 68 Gozetotide Injection upright with appropriate shielding to protect from radiation at ambient temperature (25°C (77°F); excursions permitted to 15°C to 30°C (59°F to 86°F)). Use Gallium Ga 68 Gozetotide Injection within 4 hours of preparation.

This preparation is approved for use by persons under license by the Nuclear Regulatory Commission or the relevant regulatory authority of an Agreement State.

17 PATIENT COUNSELING INFORMATION

Adequate Hydration

Instruct patients to drink a sufficient amount of water to ensure adequate hydration before their PET study and urge them to drink and urinate as often as possible during the first hours following the administration of Gallium Ga 68 Gozetotide Injection, in order to reduce radiation exposure [see Dosage and Administration (2.3) and Warnings and Precautions (5.2)].

Manufactured by:

Grand River Aseptic Manufacturing

140 Front Ave SW

Grand Rapids, MI 49504

Distributed by:

Telix Pharmaceuticals (US) Inc.

Fishers, IN 46037

PRINCIPAL DISPLAY PANEL - Kit Carton - Configuration A

NDC 74725-100-25
Rx-Only

illuccix®
(kit for the preparation of gallium
Ga 68 gozetotide Injection)

25 mcg/vial gozetotide

For Intravenous Use Only
Multiple-Dose Kit

Kit for the preparation of gallium Ga 68 gozetotide Injection
is supplied as multiple dose kit containing:

- Prescribing Information
- Diagnostic label
- Syringe label
- Vial 1 (Gozetotide vial) contains 25 mcg gozetotide vial
- Vial 2A (Acetate Buffer Vial) contains acetate buffer
- Vial 3 (Sterile Vacuumed Reaction Vial)

CONFIGURATION:
A

Configuration A is for use with
Ga 68 produced via cyclotron
or EZAG GalliaPharm®

PRINCIPAL DISPLAY PANEL - Kit Carton - Configuration B

NDC 74725-100-64

Rx Only

illuccix®
(kit for the preparation of gallium
Ga 68 gozetotide Injection)

25 mcg/vial gozetotide

For Intravenous Use Only
Multiple-Dose Kit

Kit for the preparation of gallium Ga 68 gozetotide Injection
is supplied as multiple dose kit containing:

- Prescribing Information
- Diagnostic label
- Syringe label
- Vial 1 (Gozetotide vial) contains 25 mcg gozetotide vial
- Vial 2B (Acetate Buffer Vial) contains acetate buffer
- Vial 3 (Sterile Vacuumed Reaction Vial)

CONFIGURATION:
B

Configuration B is for
use with IRE Galli Eo®